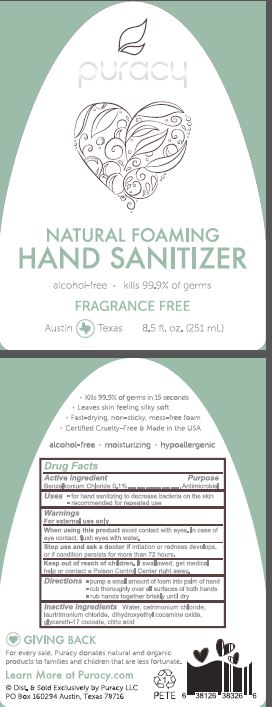 DRUG LABEL: Puracy Natural Foaming Hand Sanitizer
NDC: 72905-001 | Form: SOLUTION
Manufacturer: Puracy LLC
Category: otc | Type: HUMAN OTC DRUG LABEL
Date: 20190220

ACTIVE INGREDIENTS: BENZALKONIUM CHLORIDE 0.1 g/100 mL
INACTIVE INGREDIENTS: WATER; CETRIMONIUM CHLORIDE; LAURTRIMONIUM CHLORIDE; DIHYDROXYETHYL COCAMINE OXIDE; GLYCERETH-17 COCOATE; CITRIC ACID MONOHYDRATE

Drug Facts

Active ingredient

Benzalkonium Chloride 0.1%

Purpose

Antimicrobial

Uses

for hand sanitizing to decrease bacteria on the skin

recommended for repeated use

Warnings

For external use only

When using this product avoid contact with eyes.

In case of eye contact, flush eyes with water.

Stop use and ask a doctor if irritation or redness develops, or if condition persists for more than 72 hours.

Keep out of reach of children. If swallowed, get medical help or contact a Poison Control Center right away.

Directions

pump a small amount of foam into palm of hand

rub thoroughly over all surfaces of both hands

rub hands together briskly until dry

Inactive ingredients

Water, cetrimonium chloride, laurtrimonium chloride, dihydroxyethyl cocamine oxide, glycereth-17 cocoate, citric acid

PACKAGE LABEL

puracy

NATURAL FOAMING

HAND SANITIZER

alcohol-free kills 99.9% of germs

FRAGRANCE FREE

Austin Texas 8.5 fl.oz. (251 mL)